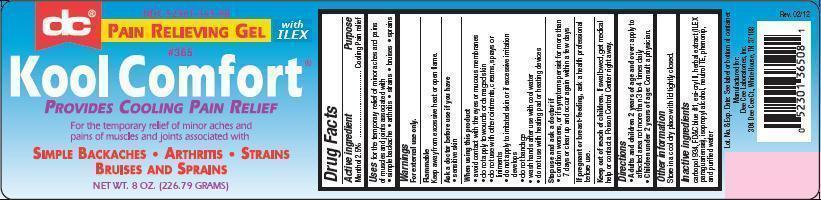 DRUG LABEL: Kool Comfort
                
NDC: 52301-365 | Form: GEL
Manufacturer: Dee Cee Laboratories, Inc.
Category: otc | Type: HUMAN OTC DRUG LABEL
Date: 20120705

ACTIVE INGREDIENTS: Menthol 2.5 g/100 g
INACTIVE INGREDIENTS: CARBOMER 934; ILEX PARAGUARIENSIS LEAF; EDETOL; WATER; ISOPROPYL ALCOHOL

Kool Comfort

Active ingredient
Menthol 2.5%

Purpose
Cooling Pain relief

Uses

For the temporary relief of minor aches and pains of muscles and joints associated with · simple backache · arthritis ·strains · bruises · sprains

Warnings

For external use only.
Flammable
Keep away from excessive heat or open flame.

Ask a doctor before use if you have

- sensitive skin

When using this product

- avoid contact with the eyes or mucous membranes
- do not apply to wounds or damaged skin
- do not use with other ointments, creams, sprays or liniments
- do not apply to irritated skin or if excessive irritation develops
- do not bandage
- wash hands after use with cool water
- do not use with heating pad or heating devices

Stop use and ask a doctor if

- condition worsens, or if symptoms persist for more than 7 days or clear up and occur again within a few days

PREGNANCY OR BREAST FEEDING

If pregnant or breast-feeding, ask a health professional before use.

Keep out of reach of children. If swallowed, get medical help or contact a Poison Control Center right away.

Directions

- Adults and children 2 years of age and over: apply to affected area not more than 3 to 4 times daily
- Children under 2 years of age: Consult a physician.

Other information

Store in a cool dry place with lid tightly closed.

Inactive ingredients

carbopol 934, FD&C blue #1, esi-cryll ll, herbal extract (ILEX paraguariensis), isopropyl alcohol, neutrol TE, phenonip, and purified water.

Lot. No. & Exp. Date: See label or bottom of container.
Manufactured for:
Dee Cee Laboratories Inc., 304 Dee Cee Ct., White House, TN 37188